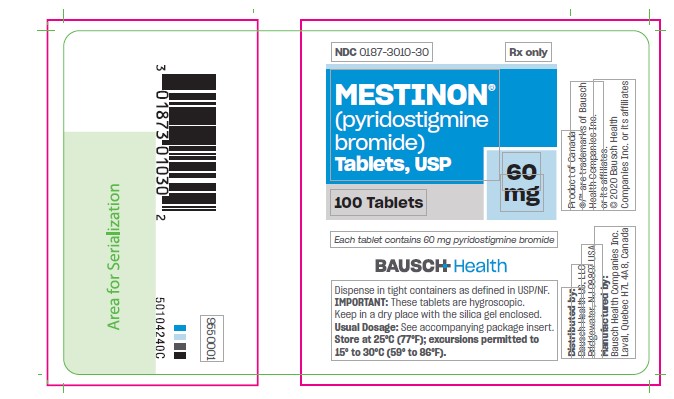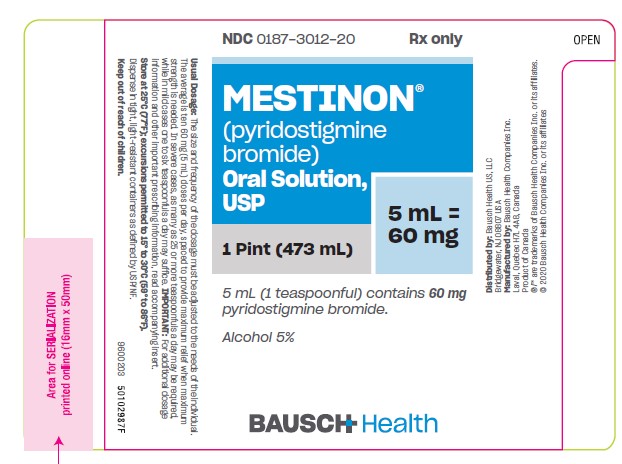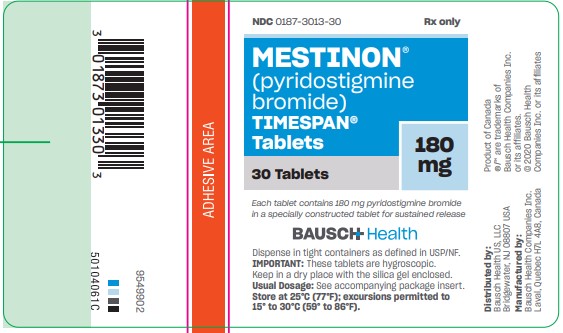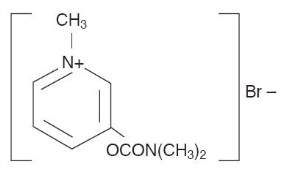 DRUG LABEL: Mestinon
NDC: 0187-3012 | Form: SOLUTION
Manufacturer: Bausch Health US, LLC
Category: prescription | Type: HUMAN PRESCRIPTION DRUG LABEL
Date: 20201202

ACTIVE INGREDIENTS: pyridostigmine bromide 60 mg/5 mL
INACTIVE INGREDIENTS: alcohol; glycerin; LACTIC ACID, UNSPECIFIED FORM; sodium benzoate; sorbitol; sucrose; FD&C Red No. 40; FD&C Blue No. 1; water

MESTINON®
(pyridostigmine bromide)
Oral Solution, USP
ORAL SOLUTION
TABLETS
and
TIMESPAN® TABLETS

DESCRIPTION:

MESTINON (pyridostigmine bromide) is an orally active cholinesterase inhibitor. Chemically, pyridostigmine bromide is 3-hydroxy-1-methylpyridinium bromide dimethylcarbamate. Its structural formula is:

MESTINON is available in the following forms: Oral Solution containing 60 mg pyridostigmine bromide per teaspoonful in a vehicle containing 5% alcohol, glycerin, lactic acid, sodium benzoate, sorbitol, sucrose, FD&C Red No. 40, FD&C Blue No. 1, flavors and water. Tablets containing 60 mg pyridostigmine bromide; each tablet also contains lactose, silicon dioxide and stearic acid. TIMESPAN tablets containing 180 mg pyridostigmine bromide; each tablet also contains carnauba wax, corn-derived proteins, isopropyl alcohol, magnesium stearate, silica gel, tribasic calcium phosphate and water.

ACTIONS:

MESTINON inhibits the destruction of acetylcholine by cholinesterase and thereby permits freer transmission of nerve impulses across the neuromuscular junction. Pyridostigmine is an analog of neostigmine (Prostigmin), but differs from it in certain clinically significant respects; for example, pyridostigmine is characterized by a longer duration of action and fewer gastrointestinal side effects.

INDICATION:

MESTINON is useful in the treatment of myasthenia gravis.

CONTRAINDICATIONS:

MESTINON is contraindicated in mechanical intestinal or urinary obstruction, and particular caution should be used in its administration to patients with bronchial asthma. Care should be observed in the use of atropine for counteracting side effects, as discussed below.

WARNINGS:

Although failure of patients to show clinical improvement may reflect underdosage, it can also be indicative of overdosage. As is true of all cholinergic drugs, overdosage of MESTINON may result in cholinergic crisis, a state characterized by increasing muscle weakness which, through involvement of the muscles of respiration, may lead to death. Myasthenic crisis due to an increase in the severity of the disease is also accompanied by extreme muscle weakness, and thus may be difficult to distinguish from cholinergic crisis on a symptomatic basis. Such differentiation is extremely important, since increases in doses of MESTINON or other drugs of this class in the presence of cholinergic crisis or of a refractory or “insensitive” state could have grave consequences. Osserman and Genkins^1 indicate that the differential diagnosis of the two types of crisis may require the use of Tensilon (edrophonium chloride) as well as clinical judgment. The treatment of the two conditions obviously differs radically. Whereas the presence of myasthenic crisis suggests the need for more intensive anticholinesterase therapy, the diagnosis of cholinergic crisis, according to Osserman and Genkins^1, calls for the prompt withdrawal of all drugs of this type. The immediate use of atropine in cholinergic crisis is also recommended.

Atropine may also be used to abolish or obtund gastrointestinal side effects or other muscarinic reactions; but such use, by masking signs of overdosage, can lead to inadvertent induction of cholinergic crisis.

For detailed information on the management of patients with myasthenia gravis, the physician is referred to one of the excellent reviews such as those by Osserman and Genkins^2, Grob^3 or Schwab.^4,5

Usage in Pregnancy:

The safety of MESTINON during pregnancy or lactation in humans has not been established. Therefore, use of MESTINON in women who may become pregnant requires weighing the drug’s potential benefits against its possible hazards to mother and child.

PRECAUTION:

Pyridostigmine is mainly excreted unchanged by the kidney.^6,7,8 Therefore, lower doses may be required in patients with renal disease, and treatment should be based on titration of drug dosage to effect.^6,7

Pediatric Use:

Safety and effectiveness in pediatric patients have not been established.

ADVERSE REACTIONS:

The side effects of MESTINON are most commonly related to overdosage and generally are of two varieties, muscarinic and nicotinic. Among those in the former group are nausea, vomiting, diarrhea, abdominal cramps, increased peristalsis, increased salivation, increased bronchial secretions, miosis and diaphoresis. Nicotinic side effects are comprised chiefly of muscle cramps, fasciculation and weakness. Muscarinic side effects can usually be counteracted by atropine, but for reasons shown in the preceding section the expedient is not without danger. As with any compound containing the bromide radical, a skin rash may be seen in an occasional patient. Such reactions usually subside promptly upon discontinuance of the medication.

To report SUSPECTED ADVERSE REACTIONS, contact Bausch Health US, LLC at 1-800-321-4576 or FDA at 1-800-FDA-1088 or www.fda.gov/medwatch.

DOSAGE AND ADMINISTRATION:

MESTINON is available in three dosage forms:

Oral Solution -

raspberry-flavored, containing 60 mg pyridostigmine bromide per teaspoonful (5 mL). This form permits accurate dosage adjustment for children and “brittle” myasthenic patients who require fractions of 60 mg doses. It is more easily swallowed, especially in the morning, by patients with bulbar involvement.

Conventional tablets -

each containing 60 mg pyridostigmine bromide.

TIMESPAN tablets -

each containing 180 mg pyridostigmine bromide. This form provides uniformly slow release, hence prolonged duration of drug action; it facilitates control of myasthenic symptoms with fewer individual doses daily. The immediate effect of a 180 mg TIMESPAN tablet is about equal to that of a 60 mg Conventional tablet; however, its duration of effectiveness, although varying in individual patients, averages 2½ times that of a 60 mg dose.

Dosage:

The size and frequency of the dosage must be adjusted to the needs of the individual patient.

Oral Solution and Conventional tablets -

The average dose is ten 60 mg tablets or ten 5 mL teaspoonfuls daily, spaced to provide maximum relief when maximum strength is needed. In severe cases as many as 25 tablets or teaspoonfuls a day may be required, while in mild cases one to six tablets or teaspoonfuls a day may suffice.

TIMESPAN tablets -

One to three 180 mg tablets, once or twice daily, will usually be sufficient to control symptoms; however, the needs of certain individuals may vary markedly from this average. The interval between doses should be at least 6 hours. For optimum control, it may be necessary to use the more rapidly acting regular tablets or oral solution in conjunction with TIMESPAN therapy.

NOTE: For information on a diagnostic test for myasthenia gravis, and for the evaluation and stabilization of therapy, please see product literature on Tensilon (edrophonium chloride).

HOW SUPPLIED:

Oral Solution, 60 mg pyridostigmine bromide per teaspoonful (5 mL) and 5% alcohol - bottles of 1 pint (473 mL) (NDC 0187-3012-20).

Tablets, are available as white, flat-faced tablets containing 60 mg pyridostigmine bromide in bottles of 100 (NDC 0187-3010-30). Each tablet is engraved “MESTINON 60 V” on one side and is quadrisect scored on the other.

TIMESPAN tablets, are available as light straw-colored, capsule-shaped tablets containing 180 mg pyridostigmine bromide in bottles of 30 (NDC 0187-3013-30).

Each tablet is engraved “MES V 180” on one side and is single-scored on the other.

Note: Because of the hygroscopic nature of the TIMESPAN tablets, mottling may occur. This does not affect their efficacy.

STORAGE AND HANDLING

Store MESTINON (pyridostigmine bromide) Oral Solution, USP, MESTINON tablets, and TIMESPAN tablets at 25°C (77°F); excursions permitted to 15° to 30°C (59° to 86°F). Keep MESTINON tablets and TIMESPAN tablets in a dry place with the silica gel enclosed.

REFERENCES:

1. Osserman KE, Genkins G. Studies in myasthenia gravis: Reduction in mortality rate after crisis. JAMA. Jan 1963; 183:97-101.
2. Osserman KE, Genkins G. Studies in myasthenia gravis. NY State J Med. June 1961; 61:2076-2085.
3. Grob D. Myasthenia gravis. A review of pathogenesis and treatment. Arch Intern Med. Oct 1961; 108:615-638.
4. Schwab RS. Management of myasthenia gravis. New Eng J Med. Mar 1963; 268:596-597.
5. Schwab RS. Management of myasthenia gravis. New Eng J Med. Mar 1963; 268:717-719.
6. Cronnelly R, Stanski DR, Miller RD, Sheiner LB. Pyridostigmine kinetics with and without renal function. Clin Pharmacol Ther. 1980; 28: No. 1, 78-81.
7. Miller RD. Pharmacodynamics and pharmacokinetics of anticholinesterase. In: Ruegheimer E, Zindler M, ed. Anesthesiology. (Hamburg, Germany: Congress; Sep 14-21, 1980; 222-223.) (Int Congr. No. 538), Amsterdam, Netherlands: Excerpta Medica; 1981.
8. Breyer-Pfaff U, Maier U, Brinkmann AM, Schumm F. Pyridostigmine kinetics in healthy subjects and patients with myasthenia gravis. Clin Pharmacol Ther. 1985; 5:495-501.

Distributed by:
Bausch Health US, LLC
Bridgewater, NJ 08807 USA

Manufactured by:
  Bausch Health Companies Inc.
  Laval, Quebec H7L 4A8, Canada
  ®/™ are trademarks of Bausch Health Companies Inc. or its affiliates.
  © 2020 Bausch Health Companies Inc. or its affiliates
  9600203 50102987F
  Rev. 12/2020

PRINCIPAL DISPLAY PANEL - 473 mL Bottle Label

NDC 0187-3012-20
Rx Only

MESTINON®
(pyridostigmine
bromide).
Oral Solution,
USP

1 Pint (473 mL)
5 mL =
60 mg

5 mL (1 teaspoonful) contains 60 mg
pyridostigmine bromide.

Alcohol 5%

BAUSCH Health

PRINCIPAL DISPLAY PANEL - 60 mg Tablets Bottle Label

NDC 0187-3010-30
Rx Only

Mestinon®
(pyridostigmine bromide)
Tablets, USP

60 mg

100 Tablets

Each tablet
contains 60 mg
pyridostigmine
bromide

BAUSCH Health

Dispense in tight containers as defined in USP/NF.

IMPORTANT: These tablets are hygrosciopic. Keep in dry place with the silica gel enclosed.
Usual Dosage: See accompanying package insert.
Store at 25°C (77°F); excursions permitted to 15° to 30°C (59° to 86°F).

PRINCIPAL DISPLAY PANEL - 180 mg Bottle Label

NDC 0187-3013-30
Rx Only
MESTINON®
(pyridostigmine
bromide)
TIMESPAN®
Tablets

180 mg

30 Tablets

Each tablet contains180 mg pyridostigmine bromide
in a specially constructed tablet for sustained release
BAUSCH Health
9549902
50104061C